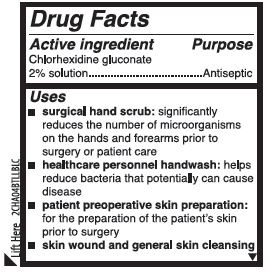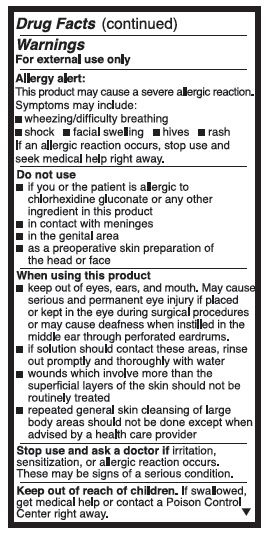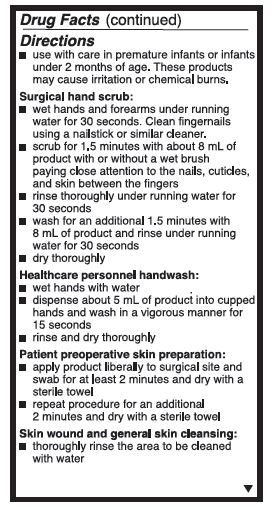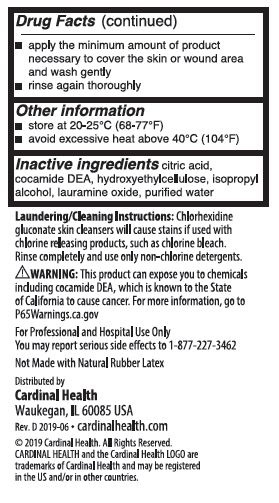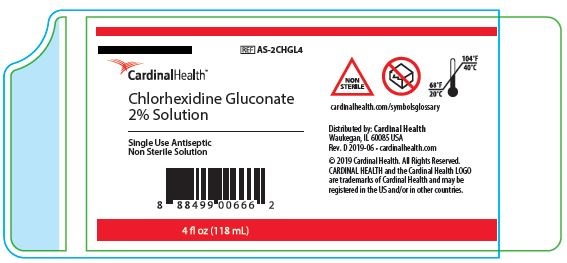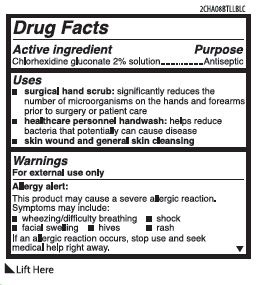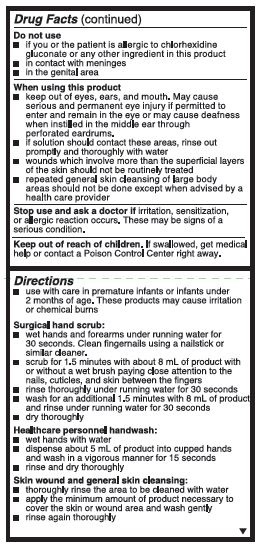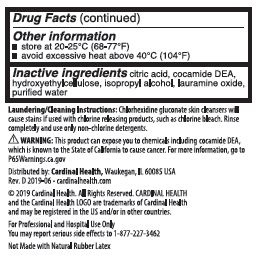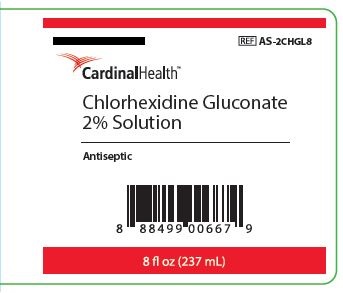 DRUG LABEL: Cardinal Health Antiseptic Skin Cleanser
NDC: 0116-0113 | Form: SOLUTION
Manufacturer: Xttrium Laboratories, Inc.
Category: otc | Type: HUMAN OTC DRUG LABEL
Date: 20250430

ACTIVE INGREDIENTS: CHLORHEXIDINE GLUCONATE 2 g/100 mL
INACTIVE INGREDIENTS: HYDROXYETHYL CELLULOSE (2000 CPS AT 1%); COCO DIETHANOLAMIDE; WATER; CITRIC ACID MONOHYDRATE; LAURAMINE OXIDE

Cardinal Health 2%

Active ingredient

Chlorhexidine gluconate 2% solution

Purpose

Antiseptic

Uses

- surgical hand scrub: significantly reduces the number of microorganisms on the hands and forearms prior to surgery or patient care
- healthcare personnel handwash: helps reduce bacteria that potentially can cause disease
- patient preoperative skin preparation: for the preparation of the patient's skin prior to surgery
- skin wound and general skin cleansing

Warnings

For external use only

Allergy alert:

This product may cause a severe allergic reaction. Symptoms may include:

- wheezing/difficulty breathing
- shock
- facial swelling
- hives
- rash

If an allergic reaction occurs, stop use and seek medical help right away.

Do not use

- if you or the patient is allergic to chlorhexidine gluconate or any other ingredient in this product
- in contact with meninges
- in the genital area
- as a preoperative skin preparation of the head or face

When using this product

- keep out of eyes, ears, and mouth. May cause serious and permanent eye injury if permitted to enter and remain in the eye or may cause deafness when instilled in the middle ear throuogh perforated eardrums.
- if solution should contact these areas, rinse out promptly and thoroughly with water
- wounds which involve more than the superficial layers of skin should not be routinely treated
- repeated general skin cleansing of large body areas should not be done except when advised by a health care provider

Stop use and ask a doctor if

irritation, sensitization, or allergic reaction occurs. These may be signs of a serious condition.

Keep out of reach of children.

If swallowed, get medical help or contact a Poison Control Center right away.

Directions

- use with care in premature infants or infants under 2 months of age. These products may cause irritation or chemical burns.

Surgical hand scrub:

- wet hands and forearms under running water for 30 seconds. Clean fingernails using a nailstick or similar cleaner.
- scrub for 1.5 minutes with about 8 mL of product with or without a wet brush paying close attention to the nails, cuticles, and skin between the fingers
- rinse thoroughly under running water for 30 seconds
- wash for an additional 1.5 minutes with 8 mL of product and rinse under running water for 30 seconds
- dry throughly

Healthcare personnel handwash:

- wet hands with water
- dispense about 5 mL of product into cupped hands and wash in a vigorous manner for 15 seconds
- rinse and dry thoroughly

Patient preoperative skin preparation:

- apply product liberally to surgical site and swab for at least 2 minutes and dry with a sterile towel
- repeat procedure for an additional 2 minutes and dry with a sterile towel

Skin wound and general skin cleansing:

- thoroughly rinse the area to be cleaned with water
- apply the minimum amount of product necessary to cover the skin or wound area and wash gently
- rinse again thoroughly

Other information

- store at 20-25°C (68-77°F)
- avoid excessive heat above 40°C (104°F)

Inactive ingredients

citric acid, cocamide DEA, hydroxyethylcellulose, isopropyl alcohol, lauramine oxide, purified water

OTHER SAFETY INFORMATION

Laudering/Cleaning Instructions: Chlorhexidine gluconate skin cleansers will cause stains if used with chlorine releasing products, such as chlorine bleach. Rinse completely and use only non-chlorine detertgents.

WARNING: This product can expose you to chemicals including cocamide DEA, which is known to the State of California to cause cancer. For more information, go to www.P65Warnings.ca.gov

For Professional and Hospital Use

You may report serious side effects to 1-877-227-3462

Not Made with Natural Rubber Latex

Distributed by

Cardinal Health

Waukegan, IL 60085 USA

Rev. D 2019-06 • cardinalhealth.com

©2019 Cardinal Health. All Rights Reserved.

CARDINAL HEALTH and the Cardinal Health LOGO are

trademarks of Cardinal Health and may be registered

in the US and/or in other countries

RECENT MAJOR CHANGES

Indications and Usage

Dosage and Administration

Package Label

NDC: 0116-0113-04

REF AS-2CHGL4

Cardinal Health

Chlorhexidine Gluconate 2% Solution

Single Use Antiseptic

Non Sterile Solution

cardinalhealth.com/symbolsglossary

Distributed by: Cardinal Health

Waukegan, IL 60085 USA

Rev. D 2019-06 • cardinalhealth.com

© 2019 Cardinal Health. All Rights Reserved.

CARDINAL HEALTH and the Cardinal Health LOGO are trademarks of Cardinal Health and may be registered in the US and/or in other countries.

4 fl oz (118 mL)

2CHA04BTLLBLC

NDC: 0116-0113-08

REF AS-2CHGL8

Cardinal Health

Chlorhexidine Gluconate 2% Solution

Antiseptic

8 fl oz (237 mL)

2CHA08BTLLBLC